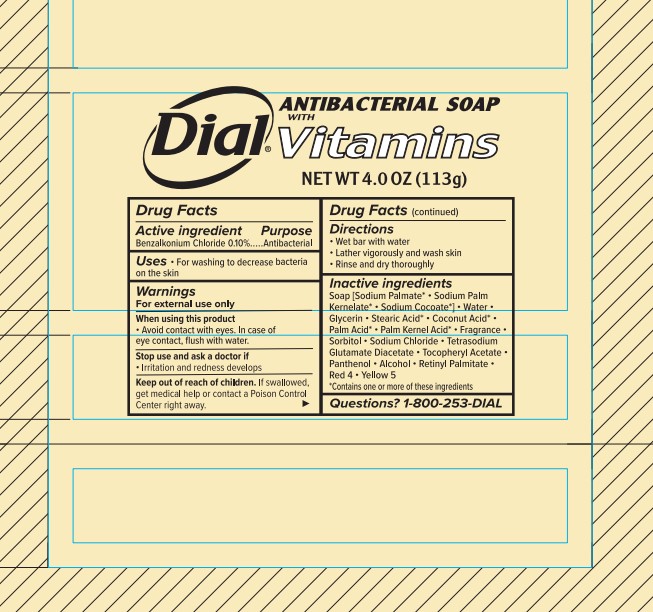 DRUG LABEL: Dial Antibacterial Vitamin Bar
NDC: 54340-286 | Form: SOAP
Manufacturer: Henkel Corporation
Category: otc | Type: HUMAN OTC DRUG LABEL
Date: 20251211

ACTIVE INGREDIENTS: BENZALKONIUM CHLORIDE 0.1 g/100 g
INACTIVE INGREDIENTS: PANTHENOL 0.024 g/100 g; RETINYL PALMITATE 0.0099 g/100 g; SORBITOL 0.6 g/100 g; TITANIUM DIOXIDE 0.8 g/100 g; SODIUM CHLORIDE 0.37 g/100 g; SODIUM PALM KERNELATE 10.54 g/100 g; GLYCERIN 7.72 g/100 g; ALCOHOL 0.01 g/100 g; SODIUM PALMATE 59.23 g/100 g; TETRASODIUM GLUTAMATE DIACETATE 0.056 g/100 g; STEARIC ACID 2.33 g/100 g; FD&C RED NO. 4 0.0002 g/100 g; FD&C YELLOW NO. 5 0.0002 g/100 g

Dial Professional Antibacterial Bar Soap with Vitamins
DIAL ANTIBACTERIAL BAR- dial vitamins antibacterial soap
Dial Vitamin Bar - 72/ 4 oz US
Dial Antibacterial Soap with Vitamins

Active Ingredient

Benzalkonium Chloride 0.10%

Purpose

Antibacterial

Uses

- for washing to decrease the bacteria on the skin

Warnings

For external use only

When using this product

- avoid contact with eyes. In case of eye contact, flush with water.

Stop using and ask doctor if

- irritation or redness develops

Keep out of reach of children.

If swallowed, get medical help or contact Poison Control Center right away.

Directions

- wet bar with water
- lather vigorously and wash skin
- rinse and dry thoroughly

Inactive ingredients

Soap[Sodium Palmate* · Sodium Palm Kernelate* · Sodium Cocoate*] · Water · Glycerin · Stearic Acid* · Coconut Acid* · Palm Acid* · Palm Kernel Acid* · Fragrance · Sorbitol · Sodium Chloride · Tetrasodium Glutamate Diacetate · Tocopheryl Acetate · Panthenol · Alcohol · Retinyl Palmidate · Red 4 · Yellow 5

*Contains one or more of these ingredients

Questions?

1-800-253-DIAL (3425)